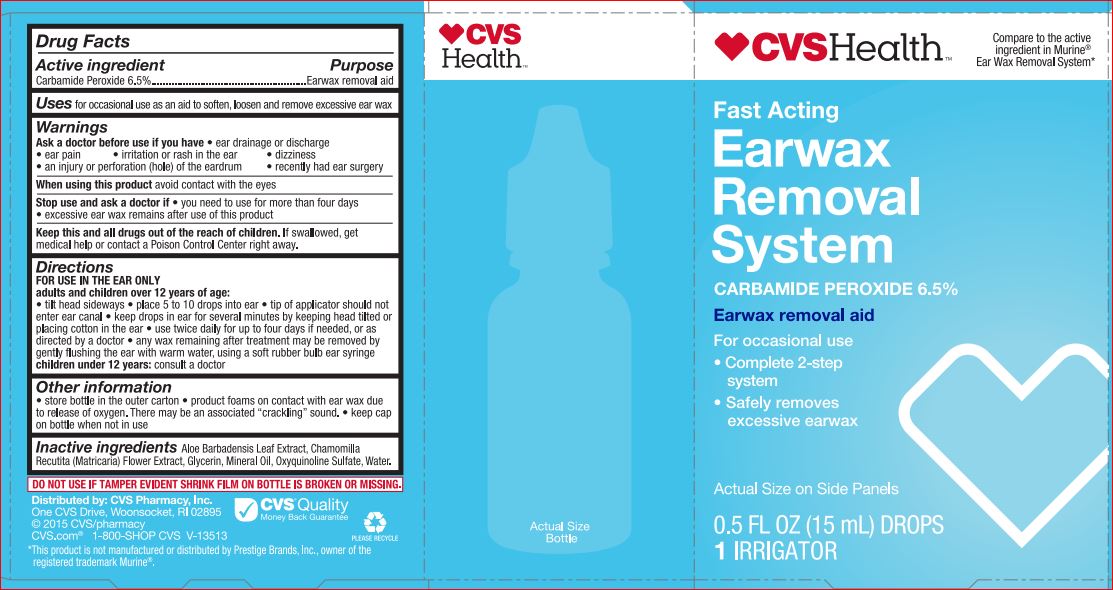 DRUG LABEL: CVS EARWAX REM
NDC: 69842-042 | Form: KIT | Route: TOPICAL
Manufacturer: CVS
Category: otc | Type: HUMAN OTC DRUG LABEL
Date: 20171120

ACTIVE INGREDIENTS: Carbamide Peroxide 6.5 g/100 mL
INACTIVE INGREDIENTS: ALOE VERA LEAF; CHAMOMILE; GLYCERIN; OXYQUINOLINE SULFATE; MINERAL OIL; WATER

EarWax Removal Drops
Drug Facts

Active ingredient

Carbamide Peroxide 6.5%

Purpose

Earwax removal aid

Uses

for occasional use as an aid to soften, loosen and remove excessive ear wax

Ask a doctor before use if you have

- ear drainage or discharge
- ear pain irritation or rash in the ear
- dizziness
- an injury or perforation (hole) of the eardrum
- recently had ear surgery

When using this product

avoid contact with the eyes

Stop use and ask a doctor if

- you need to use for more than four days
- excessive ear wax remains after use of this product

Keep this and all drugs out of the reach of children.

If swallowed, get medical help or contact a Posion Control Center right away.

Directions

FOR USE IN THE EAR ONLY

adults and children over 12 years of age:

- tilt head sideways
- palce 5 to 10 drops into ear
- tip of applicator should not enter ear canal
- keep drops in ear for several minutes by keeping head tilted or placing cotton in the ear
- use twice daily for up to four days if needed, or as directed by a doctor
- any wax remaining after treatment may be removed by gently flushing ear with warm water, using a soft rubber bulb ear syringe

children under 12 years: consult a doctor

Other information

- store bottle in the outer carton
- product foams on contact with ear wax due to release of oxygen. There may be an associated "cracklling" sound.
- keep cap on bottle when not in use

Inactive ingredients

Aloe Barbadensis Leaf Extract
Chamomilla Recutita (Matricaria) Flower Extract
Glycerin
Mineral Oil
Oxyquinoline Sulfate
Water